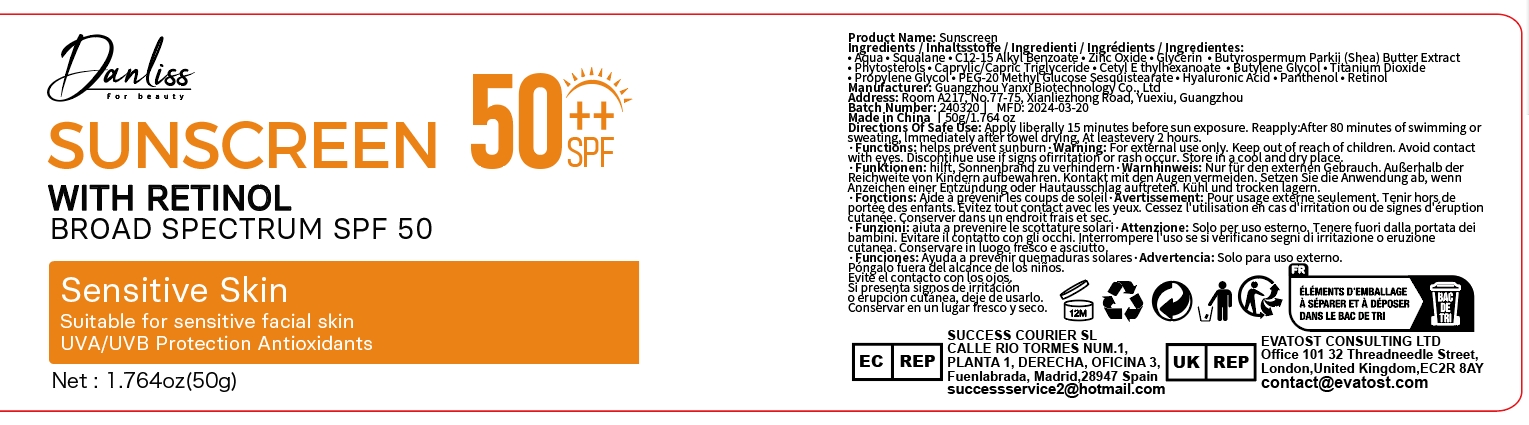 DRUG LABEL: Sunscreen
NDC: 84025-036 | Form: CREAM
Manufacturer: Guangzhou Yanxi Biotechnology Co., Ltd
Category: otc | Type: HUMAN OTC DRUG LABEL
Date: 20240508

ACTIVE INGREDIENTS: ZINC OXIDE 2 mg/50 g; SQUALANE 3 mg/50 g
INACTIVE INGREDIENTS: WATER

DOSAGE AND ADMINISTRATION

Apply liberally 15 minutes before sun exposure. Reapply: After 80 minutes of swimming or sweating, Immediately after towel drying, At least every 2 hours.

WARNINGS

For external use only.

INACTIVE INGREDIENT

WATER

INDICATIONS AND USAGE

Apply liberally 15 minutes before sun exposure. Reapply: After 80 minutes of swimming or sweating, Immediately after towel drying, At least every 2 hours.

Keep out of reach of children.

PURPOSE

helps prevent sunburn